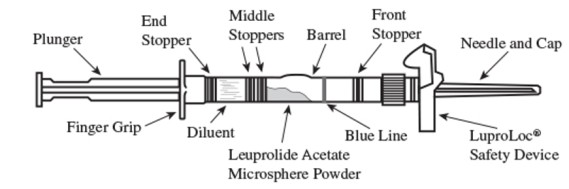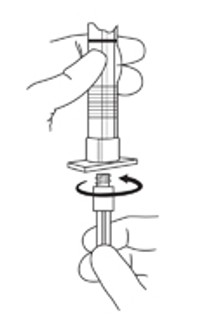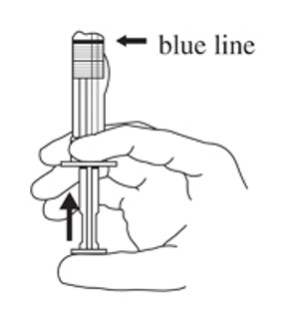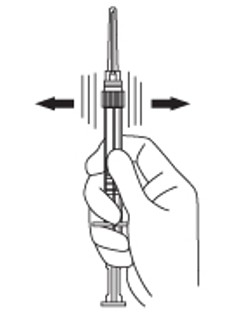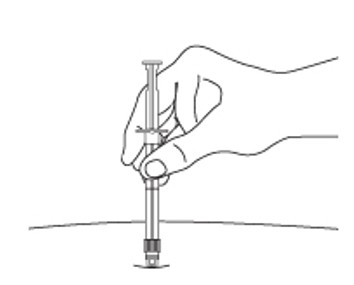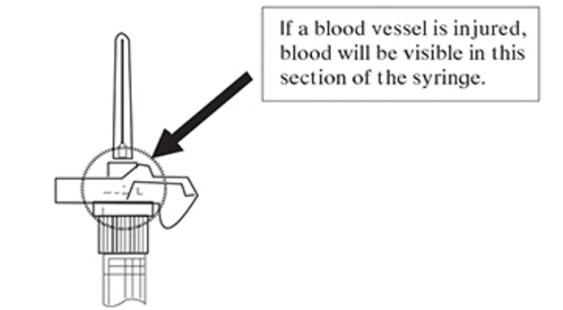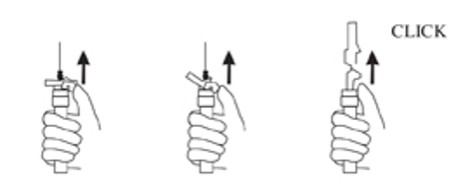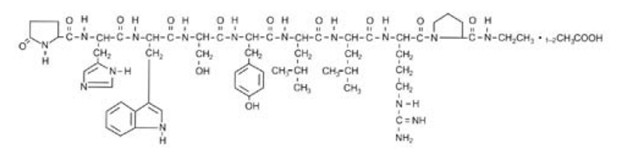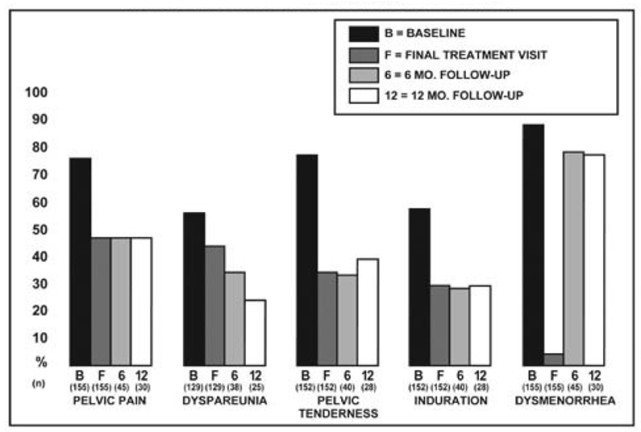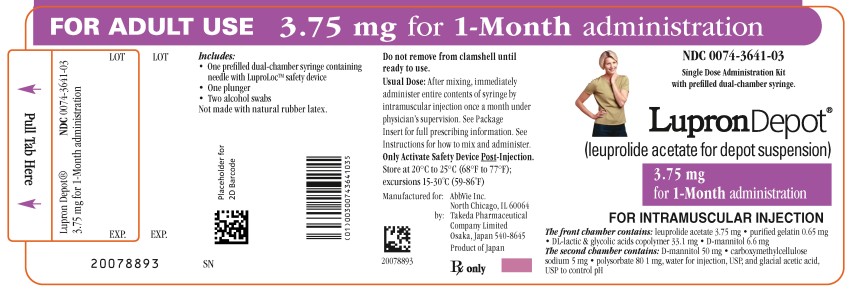 DRUG LABEL: Lupron Depot
NDC: 0074-3641 | Form: KIT | Route: INTRAMUSCULAR
Manufacturer: AbbVie Inc.
Category: prescription | Type: HUMAN PRESCRIPTION DRUG LABEL
Date: 20250918

ACTIVE INGREDIENTS: LEUPROLIDE ACETATE 3.75 mg/1 mL; ISOPROPYL ALCOHOL 0.7 mL/1 mL
INACTIVE INGREDIENTS: ACETIC ACID; WATER; POLYSORBATE 80 1 mg/1 mL; MANNITOL 56.6 mg/1 mL; GELATIN, UNSPECIFIED 0.65 mg/1 mL; CARBOXYMETHYLCELLULOSE SODIUM, UNSPECIFIED 5 mg/1 mL; WATER

HIGHLIGHTS OF PRESCRIBING INFORMATION

These highlights do not include all the information needed to use LUPRON DEPOT 3.75 mg safely and effectively. See full prescribing information for LUPRON DEPOT 3.75 mg.
LUPRON DEPOT 3.75 mg (leuprolide acetate for depot suspension) for injection, for intramuscular use
Initial U.S. Approval: 1985

RECENT MAJOR CHANGES

Warnings and Precautions, Severe Cutaneous Adverse Reactions (5.3) 9/2025

1 INDICATIONS AND USAGE

LUPRON DEPOT 3.75 mg is a gonadotropin-releasing hormone (GnRH) agonist indicated for:

Endometriosis

- Management of endometriosis, including pain relief and reduction of endometriotic lesions. (1.1)
- In combination with a norethindrone acetate for initial management of the painful symptoms of endometriosis and for management of recurrence of symptoms. (1.1)

Limitations of Use:

- The total duration of therapy with LUPRON DEPOT 3.75 mg plus add-back therapy should not exceed 12 months due to concerns about adverse impact on bone mineral density. (1.1, 2.1, 5.1)

Uterine Leiomyomata (Fibroids)

- Concomitant use with iron therapy for preoperative hematologic improvement of women with anemia caused by fibroids for whom three months of hormonal suppression is deemed necessary. (1.2)

Limitations of Use:

- LUPRON DEPOT 3.75 mg is not indicated for combination use with norethindrone acetate add-back therapy for the preoperative hematologic improvement of women with anemia caused by heavy menstrual bleeding due to fibroids. (1.2)

2 DOSAGE AND ADMINISTRATION

LUPRON DEPOT 3.75 mg for 1-month administration, given by a healthcare provider as a single intramuscular injection.

LUPRON DEPOT 3.75 mg has different release characteristics than LUPRON 11.25 mg and is dosed differently. (2.1)

- Do not substitute LUPRON DEPOT 3.75 mg for LUPRON DEPOT 11.25 mg.
- Do not administer LUPRON DEPOT 3.75 mg more frequently than once a month.
- Do not give a fractional dose of the LUPRON DEPOT 11.25 mg 3-month formulation, as it is not equivalent to a single dose of the LUPRON DEPOT 3.75 mg.
- Do not give a triple dose of the LUPRON DEPOT 3.75 mg, as it is not equivalent to a single dose of the LUPRON DEPOT 11.25 mg 3- month formulation.

Reconstitute LUPRON DEPOT 3.75 mg prior to use. (2.2)

Endometriosis:

- LUPRON DEPOT 3.75 mg administered as a single intramuscular (IM) injection once every month for up to six injections (6 months of therapy). LUPRON DEPOT may be administered alone or in combination with daily 5 mg tablet of norethindrone acetate (add-back). (2.1)
- If endometriosis symptoms recur after initial course of therapy, retreatment for no more than six months may be considered but only with the addition of norethindrone acetate add-back therapy. Do not re-treat with LUPRON DEPOT 3.75 mg alone. (2.1)

Fibroids:

- Recommended dose of LUPRON DEPOT 3.75 mg is one IM injection every month for up to three months. (2.1)

3 DOSAGE FORMS AND STRENGTHS

- Depot suspension for injection: 3.75 mg lyophilized powder for reconstitution in a dual-chamber syringe. (3)

4 CONTRAINDICATIONS

- Hypersensitivity to GnRH, GnRH agonist analogs, including leuprolide acetate, or any of the excipients in LUPRON DEPOT 3.75 mg. (4, 5.4)
- Undiagnosed abnormal uterine bleeding. (4)
- Pregnancy. (4, 8.1)

If LUPRON DEPOT 3.75 mg is administered with norethindrone acetate, the contraindications for norethindrone acetate also apply. (4)

5 WARNINGS AND PRECAUTIONS

- Loss of bone mineral density (BMD): Duration of treatment is limited by risk of bone mineral density. When using for management of endometriosis: combination use with norethindrone acetate is effective in reducing loss of BMD; do not retreat without combination norethindrone acetate. Assess BMD before retreatment. (1.1, 1.2, 5.1)
- Embryo-Fetal Toxicity: May cause fetal harm. Exclude pregnancy before initiating treatment if clinically indicated and discontinue use if pregnancy occurs. Use non-hormonal methods of contraception only. (5.2)
- Severe Cutaneous Adverse Reactions (SCARs), including Stevens-Johnson syndrome/toxic epidermal necrolysis (SJS/TEN), occurred in patients treated with LUPRON DEPOT. Discontinue LUPRON DEPOT 3.75 mg if signs or symptoms of SCARs develop. Permanently discontinue if SCARs are confirmed. (5.3)
- Hypersensitivity reactions, including anaphylaxis, have been reported with LUPRON DEPOT 3.75 mg. (5.4)
- If LUPRON is administered with norethindrone acetate, the warnings and precautions for norethindrone acetate apply to the combination regimen. (5.8)

6 ADVERSE REACTIONS

Most common adverse reactions (>10%) in clinical trials were hot flashes/sweats, headache/migraine, vaginitis, depression/emotional lability, general pain, weight gain/loss, nausea/vomiting, decreased libido, and dizziness. (6.1)

To report SUSPECTED ADVERSE REACTIONS, contact AbbVie Inc. at 1-800-633-9110 or FDA at 1-800-FDA-1088 or www.fda.gov/medwatch

FULL PRESCRIBING INFORMATION

1 INDICATIONS AND USAGE

1.1 Endometriosis

Monotherapy

LUPRON DEPOT 3.75 mg is indicated for management of endometriosis, including pain relief and reduction of endometriotic lesions.

In Combination with Norethindrone Acetate

LUPRON DEPOT 3.75 mg in combination with norethindrone acetate is indicated for initial management of the painful symptoms of endometriosis and for management of recurrence of symptoms.

Use of norethindrone acetate in combination with LUPRON DEPOT 3.75 mg is referred to as add-back therapy, and is intended to reduce the loss of bone mineral density (BMD) and reduce vasomotor symptoms associated with use of LUPRON DEPOT 3.75 mg.

Limitations of Use:

The total duration of therapy with LUPRON DEPOT 3.75 mg plus add-back therapy should not exceed 12 months due to concerns about adverse impact on bone mineral density [see Dosage and Administration (2.1) and Warnings and Precautions (5.1)].

1.2 Uterine Leiomyomata (Fibroids)

LUPRON DEPOT 3.75 mg, used concomitantly with iron therapy, is indicated for the preoperative hematologic improvement of women with anemia caused by fibroids for whom three months of hormonal suppression is deemed necessary.

Consider a one-month trial period on iron alone, as some women will respond to iron alone [see Clinical Studies (14.2)]. LUPRON DEPOT 3.75 mg may be added if the response to iron alone is considered inadequate.

Limitations of Use:

LUPRON DEPOT 3.75 mg is not indicated for combination use with norethindrone acetate add-back therapy for the preoperative hematologic improvement of women with anemia caused by heavy menstrual bleeding due to fibroids [see Dosage and Administration (2.1)].

2 DOSAGE AND ADMINISTRATION

2.1 Important Use Information

LUPRON DEPOT 3.75 mg must be administered by a healthcare professional.

LUPRON DEPOT 3.75 mg for 1-month administration has different release characteristics than LUPRON 11.25 mg for 3-month administration and is dosed differently.

- Do not substitute LUPRON DEPOT 3.75 mg for LUPRON DEPOT 11.25 mg.
- Do not administer LUPRON DEPOT 3.75 mg more frequently than once a month.
- Do not give a fractional dose of the LUPRON DEPOT 11.25 mg 3-month formulation as it is not equivalent to a single dose of the LUPRON DEPOT 3.75 mg.
- Do not give a triple dose of the LUPRON DEPOT 3.75 mg, as it is not equivalent to a single dose of the LUPRON DEPOT 11.25 mg 3-month formulation.

Endometriosis

The initial and retreatment dosage regimens for LUPRON DEPOT 3.75 mg for the management of women with endometriosis are outlined in Table 1.

Table 1. LUPRON DEPOT 3.75 mg, Management of Endometriosis
Treatment Phase | LUPRON DEPOT 3.75 mg Dosing | Maximum Treatment Duration
Initial Treatment^1 | 3.75 mg IM every 1 month for 1 to 6 doses | 6 months
Retreatment^2 | 3.75 mg IM every 1 month for 1 to 6 doses | 6 months
 |  | 12 MONTHS^3 TOTAL TREATMENT DURATION

^1May use LUPRON DEPOT 3.75 mg with or without norethindrone acetate 5 mg tablet taken daily.

^2Use LUPRON DEPOT 3.75 mg with norethindrone acetate for retreatment 5 mg tablet taken daily [see Warnings and Precautions (5.1)] and assess bone mineral density (BMD) prior to retreatment.

^3Treatment should not exceed 12 months due to concerns about adverse impact on bone mineral density.

Fibroids

The recommended dosage of LUPRON DEPOT 3.75 mg is one IM injection every month for up to three months.

2.2 Reconstitution and Administration for Injection of LUPRON DEPOT

- Reconstitute and administer the lyophilized microsphere as a single IM injection as directed below. Visually inspect the drug product for particulate matter and discoloration prior to administration, whenever solution and container permit.
- Inject the LUPRON DEPOT 3.75 mg suspension immediately or discard if not used within two hours as the suspension does not contain a preservative.

1. Visually inspect the LUPRON DEPOT 3.75 mg powder. Do not use the syringe if clumping or caking is evident. A thin layer of powder on the wall of the syringe is considered normal prior to mixing with the diluent. The diluent should appear clear.

2. To prepare for injection, screw the white plunger into the end stopper until the stopper begins to turn (see Figure A and Figure B).

Figure A:

Figure B:

3. Hold the syringe UPRIGHT. Release the diluent by SLOWLY PUSHING the plunger for 6 to 8 seconds until the first middle stopper is at the blue line in the middle of the barrel (see Figure C).

Figure C:

4. Keep the syringe upright. Mix the microsphere powder thoroughly by gently shaking the syringe until the powder forms a uniform suspension. The suspension will appear milky. If the powder adheres to the stopper or caking/clumping is present, tap the syringe with your finger to disperse. Do not use if any of the powder has not gone into suspension (see Figure D).

Figure D:

5. Keep the syringe upright. With the opposite hand pull the needle cap upward without twisting.

6. Keep the syringe upright. Advance the plunger to expel the air from the syringe. The syringe is now ready for injection.

7. After cleaning the injection site with an alcohol swab, administer the IM injection by inserting the needle at a 90-degree angle into the gluteal area, anterior thigh, or deltoid. Injection sites should be alternated (see Figure E).

Figure E:

Note: If a blood vessel is accidentally penetrated, aspirated blood will be visible just below the luer lock (see Figure F) and can be seen through the transparent LuproLoc® safety device. If blood is present, remove the needle immediately. Do not inject the medication.

Figure F:

8. Inject the entire contents of the syringe intramuscularly.

9. Withdraw the needle. Once the syringe has been withdrawn, immediately activate the LuproLoc® safety device by pushing the arrow on the lock upward towards the needle tip with the thumb or finger, as illustrated, until the needle cover of the safety device over the needle is fully extended and a click is heard or felt (see Figure G).

Figure G:

10. Dispose of the syringe according to local regulations/procedures.

3 DOSAGE FORMS AND STRENGTHS

For Injection: 3.75 mg of leuprolide acetate as a white lyophilized microsphere powder for reconstitution in a single dose prefilled dual chamber syringe; with one chamber containing the lyophilized powder and the other chamber containing the clear diluent.

4 CONTRAINDICATIONS

LUPRON DEPOT 3.75 mg is contraindicated in women with the following:

- Hypersensitivity to gonadotropin-releasing hormone (GnRH), GnRH agonist analogs, including leuprolide acetate, or any of the excipients in LUPRON DEPOT 3.75 mg [see Warnings and Precautions (5.4) and Adverse Reactions (6.2)]
- Undiagnosed abnormal uterine bleeding
- Pregnancy [see Warnings and Precautions (5.2) and Use in Specific Populations (8.1)]

When norethindrone acetate is administered with LUPRON DEPOT 3.75 mg, the contraindications to the use of norethindrone acetate also apply to this combination regimen. Refer to the norethindrone acetate prescribing information for a list of contraindications for norethindrone acetate.

5 WARNINGS AND PRECAUTIONS

5.1 Loss of Bone Mineral Density

LUPRON DEPOT 3.75 mg induces a hypoestrogenic state that results in loss of bone mineral density (BMD), some of which may not be reversible after stopping treatment. In women with major risk factors for decreased BMD such as chronic alcohol use (> 3 units per day), tobacco use, strong family history of osteoporosis, or chronic use of drugs that can decrease BMD, such as anticonvulsants or corticosteroids, use of LUPRON DEPOT 3.75 mg may pose an additional risk. Carefully weigh the risks and benefits of LUPRON DEPOT 3.75 mg use in these populations.

The duration of LUPRON DEPOT 3.75 mg treatment is limited by the risk of loss of bone mineral density [see Dosage and Administration (2.1)].

When using LUPRON DEPOT 3.75 mg for the management of endometriosis, combination use of norethindrone acetate (add-back therapy) is effective in reducing the loss of BMD that occurs with leuprolide acetate [see Clinical Studies (14.2)]. Do not retreat with LUPRON DEPOT 3.75 mg without combination norethindrone acetate. Assess BMD before retreatment.

5.2 Embryo-Fetal Toxicity

Based on animal reproduction studies and the drug’s mechanism of action, LUPRON DEPOT 3.75 mg may cause fetal harm if administered to a pregnant woman and is contraindicated in pregnant women. Exclude pregnancy prior to initiating treatment with LUPRON DEPOT 3.75 mg if clinically indicated. Discontinue LUPRON DEPOT 3.75 mg if the woman becomes pregnant during treatment and inform the woman of potential risk to the fetus [see Contraindications (4) and Use in Specific Populations (8.1)]. Advise women to notify their healthcare provider if they believe they may be pregnant.

When used at the recommended dose and dosing interval, LUPRON DEPOT 11.25 mg usually inhibits ovulation and stops menstruation. Contraception, however, is not ensured by taking LUPRON DEPOT 11.25 mg. If contraception is indicated, advise women to use non-hormonal methods of contraception while on treatment with LUPRON DEPOT 3.75 mg.

5.3 Severe Cutaneous Adverse Reactions

Severe cutaneous adverse reactions (SCARs) have been reported in patients receiving GnRH agonists, including LUPRON DEPOT. These reactions include Stevens-Johnson syndrome/toxic epidermal necrolysis (SJS/TEN), drug reaction with eosinophilia and systemic symptoms (DRESS), and acute generalized exanthematous pustulosis (AGEP), including cases with visceral involvement and/or requiring skin grafts [see Adverse Reactions (6.2)].

Monitor patients for the signs and symptoms of SCARs such as fever, flu-like symptoms, mucosal lesions, progressive skin rash, or lymphadenopathy. Advise patients of the signs and symptoms of SCARs.

If a SCAR is suspected, discontinue LUPRON DEPOT 3.75 mg. Consult with a healthcare provider with expertise in the diagnosis and management of SCARs. If a diagnosis of SCAR is confirmed, permanently discontinue LUPRON DEPOT 3.75 mg.

5.4 Hypersensitivity Reactions

Hypersensitivity reactions, including anaphylaxis, have been reported with LUPRON DEPOT use. LUPRON DEPOT 3.75 mg is contraindicated in women with a history of hypersensitivity to gonadotropin-releasing hormone (GnRH) or GnRH agonist analogs [see Contraindications (4) and Adverse Reactions (6.2)].

In clinical trials of LUPRON DEPOT 3.75 mg, adverse events of asthma were reported in women with pre-existing histories of asthma, sinusitis, and environmental or drug allergies. Symptoms consistent with an anaphylactoid or asthmatic process have been reported postmarketing.

5.5 Initial Flare of Symptoms

Following the first dose of LUPRON DEPOT 3.75 mg, sex steroids temporarily rise above baseline because of the physiologic effect of the drug. Therefore, an increase in symptoms may be observed during the initial days of therapy, but these should dissipate with continued therapy.

5.6 Convulsions

There have been postmarketing reports of convulsions in women on GnRH agonists, including leuprolide acetate. These included women with and without concurrent medications and comorbid conditions.

5.7 Clinical Depression

Depression may occur or worsen during treatment with GnRH agonists including LUPRON DEPOT 3.75 mg [see Adverse Reactions (6.1)]. Carefully observe women for depression, especially those with a history of depression and consider whether the risks of continuing LUPRON DEPOT 3.75 mg outweigh the benefits. Women with new or worsening depression should be referred to a mental health professional, as appropriate.

5.8 Risks Associated with Norethindrone Combination Treatment

If LUPRON DEPOT 3.75 mg is administered with norethindrone acetate, the warnings and precautions for norethindrone acetate apply to this regimen. Refer to the norethindrone acetate prescribing information for a full list of the warnings and precautions for norethindrone acetate.

6 ADVERSE REACTIONS

The following clinically significant adverse reactions are described elsewhere in the labeling:

- Loss of Bone Mineral Density [see Warnings and Precautions (5.1)]
- Severe Cutaneous Adverse Reactions [see Warnings and Precautions (5.3)]
- Hypersensitivity Reactions [see Warnings and Precautions (5.4)]
- Initial Flare of Symptoms with Management of Endometriosis [see Warnings and Precautions (5.5)]
- Convulsions [see Warnings and Precautions (5.6)]
- Clinical Depression [see Warnings and Precautions (5.7)]

6.1 Clinical Trials Experience

Because clinical trials are conducted under widely varying conditions, adverse reaction rates observed in the clinical trials of a drug cannot be directly compared to rates in the clinical trials of another drug and may not reflect the rates observed in clinical practice.

LUPRON DEPOT 3.75 mg (Monotherapy)

The safety of LUPRON DEPOT 3.75 mg for the endometriosis and fibroids indications was established based on adequate and well-controlled adult studies. The safety of LUPRON DEPOT 3.75 mg was evaluated in six clinical studies in which a total of 332 women were treated for up to six months. Women were treated with monthly IM injections of LUPRON DEPOT 3.75 mg. The population age range was 18 to 53 years old.

Adverse Reactions (>1%) Leading to Study Discontinuation

In the six studies 1.8% of women treated with LUPRON DEPOT 3.75 mg discontinued prematurely due to hot flashes.

Common Adverse Reactions

The safety of LUPRON DEPOT 3.75 mg was evaluated in controlled clinical trials in 166 women with endometriosis and 166 women with uterine fibroids. Adverse reactions reported in ≥ 5% of women in either of these populations are noted in Tables 2 and 3, below.

Table 2. Adverse Reactions Reported in ≥ 5% of Women with Endometriosis Taking LUPRON DEPOT 3.75 mg - 2 Studies
 | LUPRON DEPOT 3.75 mg N=166 | Danazol N=136 | Placebo N=31
 | % | % | %
Hot flashes/sweats* | 84 | 57 | 29
Headache* | 32 | 22 | 6
Vaginitis* | 28 | 17 | 0
Depression/emotional lability* | 22 | 20 | 3
General pain | 19 | 16 | 3
Weight gain/loss | 13 | 26 | 0
Nausea/vomiting | 13 | 13 | 3
Decreased libido* | 11 | 4 | 0
Dizziness | 11 | 3 | 0
Acne | 10 | 20 | 0
Skin reactions | 10 | 15 | 3
Joint disorder* | 8 | 8 | 0
Edema | 7 | 13 | 3
Paresthesias | 7 | 8 | 0
GI disturbances* | 7 | 6 | 3
Neuromuscular disorders* | 7 | 13 | 0
Breast changes/tenderness/pain* | 6 | 9 | 0
Nervousness* | 5 | 8 | 0
In these same studies, symptoms reported in < 5% of women included:
- Body as a Whole - Injection site reactions
- Cardiovascular System - Palpitations, syncope, tachycardia
- Digestive System - Appetite changes, dry mouth, thirst
- Endocrine System - Androgen-like effects, lactation
- Blood and Lymphatic System - Ecchymosis
- Nervous/Psychiatric System - Anxiety*, insomnia/sleep disorders*, delusions, memory disorder, personality disorder
- Dermal System - Alopecia, hair disorder
- Ocular system - Ophthalmologic disorders*
- Urogenital System - Dysuria*.
  * = Possible effect of decreased estrogen.

Table 3. Adverse Reactions Reported in ≥ 5% of Women with Uterine Fibroids (4 Studies) Taking LUPRON DEPOT 3.75 mg
 | LUPRON DEPOT 3.75 mg N=166 | Placebo N=163
 | % | %
Hot flashes/sweats* | 73 | 18
Headache* | 26 | 18
Vaginitis* | 11 | 2
Depression/emotional lability* | 11 | 4
Asthenia | 8 | 5
General pain | 8 | 6
Joint disorder* | 8 | 3
Edema | 5 | 1
Nausea/vomiting | 5 | 4
Nervousness* | 5 | 1
In these same studies, symptoms reported in < 5% of women included:
- Body as a Whole - Body odor, flu syndrome, injection site reactions
- Cardiovascular System - Tachycardia
- Digestive System - Appetite changes, dry mouth, taste perversion
- Endocrine System - Androgen-like effects, menstrual disorders
- Nervous/Psychiatric System - Anxiety*, insomnia/sleep disorders*
- Respiratory System - Rhinitis
- Dermal System - Nail disorder
- Ocular system - Conjunctivitis
  * = Possible effect of decreased estrogen.

In one controlled clinical trial utilizing the monthly formulation of LUPRON DEPOT 3.75 mg and LUPRON DEPOT 7.5 mg in women diagnosed with uterine fibroids received one injection every 4 weeks for a duration of 12 weeks. Adverse reactions of galactorrhea, pyelonephritis, and urinary incontinence were reported in the 7.5 mg dose group but not in the 3.75 mg dose group. Generally, a higher incidence of hypoestrogenic effects was observed at the higher dose.

LUPRON DEPOT 3.75 mg in combination with Norethindrone Acetate 5 mg

The safety of co-administering LUPRON DEPOT 3.75 mg and norethindrone acetate was evaluated in two clinical studies in which a total of 242 women with endometriosis were treated for up to one year. Women were treated with monthly IM injections of LUPRON DEPOT 3.75 mg (13 injections) alone or monthly IM injections of LUPRON DEPOT 3.75 mg (13 injections) plus norethindrone acetate 5 mg daily. The population age range was 17 to 43 years old. The majority of women were Caucasian (87%).

In one study, 106 women were randomized to one year of treatment with LUPRON DEPOT 3.75 mg alone or with LUPRON DEPOT 3.75 mg and norethindrone acetate. The other study was an open-label, single arm clinical study in 136 women on one year of treatment with LUPRON DEPOT 3.75 mg plus norethindrone acetate, with follow-up for up to 12 months after completing treatment.

Adverse Reactions (>1%) Leading to Study Discontinuation

In the controlled study, 18% of women treated monthly with LUPRON DEPOT 3.75 mg and 18% of women treated monthly with LUPRON DEPOT 3.75 mg plus norethindrone acetate discontinued therapy due to adverse reactions, most commonly hot flashes (6%) and insomnia (4%) in the LUPRON DEPOT 3.75 mg alone group and hot flashes and emotional lability (4% each) in the LUPRON DEPOT 3.75 mg plus norethindrone group.

In the open-label study, 13% of women treated monthly with LUPRON DEPOT 3.75 mg plus norethindrone acetate discontinued therapy due to adverse reactions, most commonly depression (4%) and acne (2%).

Common Adverse Reactions

Table 4 lists the adverse reactions observed in at least 5% of women in any treatment group, during the first 6 months of treatment in the two add-back clinical studies, in which women were treated with monthly LUPRON DEPOT 3.75 mg with or without norethindrone acetate 5 mg daily co-treatment. The most frequently-occurring adverse reactions observed in these studies were hot flashes and headaches.

Table 4. Adverse Reactions Occurring in the First Six Months of Treatment in ≥ 5% of Women with Endometriosis
 | Controlled Study |  | Open Label Study
 | LD-Only* | LD/N† | LD/N†
 | N=51 | N=55 | N=136
Adverse Reactions | % | % | %
Any Adverse Reaction | 98 | 96 | 93
Hot flashes/Sweats | 98 | 87 | 57
Headache/Migraine | 65 | 51 | 46
Depression/Emotional Lability | 31 | 27 | 34
Insomnia/Sleep Disorder | 31 | 13 | 15
Nausea/Vomiting | 25 | 29 | 13
Pain | 24 | 29 | 21
Vaginitis | 20 | 15 | 8
Asthenia | 18 | 18 | 11
Dizziness/Vertigo | 16 | 11 | 7
Altered Bowel Function (constipation, diarrhea) | 14 | 15 | 10
Weight Gain | 12 | 13 | 4
Decreased Libido | 10 | 4 | 7
Nervousness/Anxiety | 8 | 4 | 11
Breast Changes/Pain/Tenderness | 6 | 13 | 8
Memory Disorder | 6 | 2 | 4
Skin/Mucous Membrane Reaction | 4 | 9 | 11
GI Disturbance (dyspepsia, flatulence) | 4 | 7 | 4
Androgen-Like Effects (acne, alopecia) | 4 | 5 | 18
Changes in Appetite | 4 | 0 | 6
Injection Site Reaction | 2 | 9 | 3
Neuromuscular Disorder (leg cramps, paresthesia) | 2 | 9 | 3
Menstrual Disorders | 2 | 0 | 5
Edema | 0 | 9 | 7
* LD-Only = LUPRON DEPOT 3.75 mg
† LD/N = LUPRON DEPOT 3.75 mg plus norethindrone acetate 5 mg

In the controlled clinical trial, 50 of 51 (98%) women in the LUPRON DEPOT 3.75 mg arm and 48 of 55 (87%) women in the LUPRON DEPOT 3.75 mg plus norethindrone acetate arm reported experiencing hot flashes on one or more occasions during treatment.

Table 5 presents hot flash data in the last month of treatment.

Table 5. Hot Flashes in the Month Prior to the Assessment Visit (Controlled Study)
Assessment Visit | Treatment Group | Number of Women Reporting Hot Flashes |  | Number of Days with Hot Flashes |  | Maximum Number Hot Flashes in 24 Hours
 |  | N | (%) | N^2 | Mean | N^2 | Mean
Week 24 | LD-Only* | 32/37 | 86 | 37 | 19 | 36 | 5.8
 | LD/N† | 22/38 | 58^1 | 38 | 7^1 | 38 | 1.9^1
* LD-Only = LUPRON DEPOT 3.75 mg.
† LD/N = LUPRON DEPOT 3.75 mg plus norethindrone acetate 5 mg.
^1Statistically significantly less than the LD-Only group (p<0.01).
^2Number of women assessed.

Serious Adverse Reactions

Urinary tract infection (1.9%), renal calculus (0.7%), depression (0.7%)

Changes in Laboratory Values during Treatment

Liver Enzymes

Three percent of women with uterine fibroids treated with LUPRON DEPOT 3.75 mg, manifested post-treatment transaminase values that were at least twice the baseline value and above the upper limit of the normal range.

In the two clinical trials of women with endometriosis, 2% (4 of 191) women receiving leuprolide acetate plus norethindrone acetate for up to 12 months developed an elevated (at least twice the upper limit of normal) SGPT and 1% (2 of 136) developed an elevated GGT. Among these six women with increased liver tests, the increases in five were observed beyond 6 months of treatment. None were associated with an elevated bilirubin concentration.

Lipids

Triglycerides were increased above the upper limit of normal in 12% of the women with endometriosis who received LUPRON DEPOT 3.75 mg.

Of those women with endometriosis and women with uterine fibroid whose pretreatment cholesterol values were in the normal range, mean change following therapy was +16 mg/dL to +17 mg/dL in women with endometriosis and +11 mg/dL to +29 mg/dL in women with uterine fibroids. In the women with endometriosis, increases from the pretreatment values were statistically significant (p<0.03). There was essentially no increase in the LDL/HDL ratio in women from either population receiving LUPRON DEPOT 3.75 mg.

Percent changes from baseline for serum lipids and percentages of women with serum lipid values outside of the normal range in the two studies of LUPRON DEPOT 3.75 mg and norethindrone acetate are summarized in Table 6 and Table 7 below. The major impact of adding norethindrone acetate to treatment with LUPRON DEPOT 3.75 mg was a decrease in serum HDL cholesterol and an increase in the LDL/HDL ratio.

Table 6. Serum Lipids: Mean Percent Changes from Baseline Values at Treatment Week 24
 | LUPRON DEPOT 3.75 mg |  | LUPRON DEPOT 3.75 mg plus norethindrone acetate 5 mg daily
 | Controlled Study (n=39) |  | Controlled Study (n=41) |  | Open Label Study (n=117)
 | Baseline Value* | Week 24 % Change | Baseline Value* | Week 24 % Change | Baseline Value* | Week 24 % Change
Total Cholesterol | 170.5 | 9.2% | 179.3 | 0.2% | 181.2 | 2.8%
HDL Cholesterol | 52.4 | 7.4% | 51.8 | -18.8% | 51.0 | -14.6%
LDL Cholesterol | 96.6 | 10.9% | 101.5 | 14.1% | 109.1 | 13.1%
LDL/HDL Ratio | 2.0† | 5.0% | 2.1† | 43.4% | 2.3† | 39.4%
Triglycerides | 107.8 | 17.5% | 130.2 | 9.5% | 105.4 | 13.8%
* mg/dL
† ratio

Changes from baseline tended to be greater at Week 52. After treatment, mean serum lipid levels from women with follow-up data returned to pretreatment values.

Table 7. Percentage of Women with Serum Lipids Values Outside of the Normal Range
 | LUPRON DEPOT 3.75 mg |  | LUPRON DEPOT 3.75 mg plus norethindrone acetate 5 mg daily
 | Controlled Study (n=39) |  | Controlled Study (n=41) |  | Open Label Study (n=117)
 | Week 0 | Week 24* | Week 0 | Week 24* | Week 0 | Week 24*
Total Cholesterol (>240 mg/dL) | 15% | 23% | 15% | 20% | 6% | 7%
HDL Cholesterol (<40 mg/dL) | 15% | 10% | 15% | 44% | 15% | 41%
LDL Cholesterol (>160 mg/dL) | 0% | 8% | 5% | 7% | 9% | 11%
LDL/HDL Ratio (>4.0) | 0% | 3% | 2% | 15% | 7% | 21%
Triglycerides (>200 mg/dL) | 13% | 13% | 12% | 10% | 5% | 9%
* Includes all women regardless of baseline value.

6.2 Postmarketing Experience

The following adverse reactions have been identified during post-approval use of LUPRON DEPOT monotherapy or LUPRON DEPOT with norethindrone acetate add-back therapy. Because these reactions are reported voluntarily from a population of uncertain size, it is not always possible to reliably estimate their frequency or establish a causal relationship to drug exposure.

During postmarketing surveillance which includes other dosage forms and other populations, the following adverse reactions were reported:

- Skin and Subcutaneous Tissue: rash, urticaria, photosensitivity, erythema multiforme, bullous dermatitis, dermatitis exfoliative, drug reaction with eosinophilia and systemic symptoms (DRESS), Stevens-Johnson syndrome/toxic epidermal necrolysis (SJS/TEN), and acute generalized exanthematous pustulosis (AGEP)
- Body as a whole: Hypersensitivity reactions including anaphylaxis
- Nervous/Psychiatric System: Mood swings, including depression; suicidal ideation and attempt; convulsion, peripheral neuropathy, paralysis
- Hepato-biliary system: Serious liver injury
- General disorders and administration site conditions: Injection site reactions including induration, abscess, and necrosis
- Injury, poisoning and procedural complications: Spinal fracture
- Investigations: Decreased white blood count
- Musculoskeletal and connective tissue system: Tenosynovitis-like symptoms
- Vascular system: Hypotension, hypertension, deep vein thrombosis, pulmonary embolism, myocardial infarction, stroke, transient ischemic attack
- Respiratory system: Symptoms consistent with an asthmatic process
- Multi-system disorders: Symptoms consistent with fibromyalgia (e.g., joint and muscle pain, headaches, sleep disorders, gastrointestinal distress, and shortness of breath), individually and collectively.

Pituitary apoplexy

During postmarketing surveillance, cases of pituitary apoplexy (a clinical syndrome secondary to infarction of the pituitary gland) have been reported after the administration of leuprolide acetate and other GnRH agonists. In a majority of these cases, a pituitary adenoma was diagnosed, with a majority of pituitary apoplexy cases occurring within 2 weeks of the first dose, and some within the first hour. In these cases, pituitary apoplexy has presented as sudden headache, vomiting, visual changes, ophthalmoplegia, altered mental status, and sometimes cardiovascular collapse. Immediate medical attention has been required.

7 DRUG INTERACTIONS

No drug-drug interaction studies have been conducted with LUPRON DEPOT 3.75 mg.

8 USE IN SPECIFIC POPULATIONS

8.1 Pregnancy

Risk Summary

LUPRON DEPOT 3.75 mg is contraindicated in pregnancy [see Contraindications (4)].

LUPRON DEPOT 3.75 mg may cause fetal harm based on findings from animal studies and the drug’s mechanism of action [see Clinical Pharmacology (12.1)]. There are limited human data on the use of LUPRON DEPOT in pregnant women. Based on animal reproduction studies, LUPRON DEPOT 3.75 mg may be associated with an increased risk of pregnancy complications, including early pregnancy loss and fetal harm. In animal reproduction studies, subcutaneous administration of leuprolide acetate to rabbits during the period of organogenesis caused embryo-fetal toxicity, decreased fetal weights and a dose-dependent increase in major fetal abnormalities in animals at doses less than the recommended human dose based on body surface area using an estimated daily dose. A similar rat study also showed increased fetal mortality and decreased fetal weights but no major fetal abnormalities at doses less than the recommended human dose based on body surface area using an estimated daily dose [see Data].

Data

Animal Data

When administered on day 6 of pregnancy at test dosages of 0.00024 mg/kg, 0.0024 mg/kg, and 0.024 mg/kg (1/300 to 1/3 of the human dose) to rabbits, leuprolide acetate produced a dose-related increase in major fetal abnormalities. Similar studies in rats failed to demonstrate an increase in fetal malformations. There was increased fetal mortality and decreased fetal weights with the two higher doses of LUPRON DEPOT in rabbits and with the highest dose (0.024 mg/kg) in rats.

8.2 Lactation

Risk Summary

There are no data on the presence of leuprolide acetate in either animal or human milk, the effects on the breastfed infants, or the effects on milk production.

The developmental and health benefits of breastfeeding should be considered along with the mother’s clinical need for LUPRON DEPOT 3.75 mg and any potential adverse effects on the breastfed infant from LUPRON DEPOT 3.75 mg or from the underlying maternal condition.

8.3 Females and Males of Reproductive Potential

Pregnancy Testing

Exclude pregnancy in women of reproductive potential prior to initiating LUPRON DEPOT 3.75 mg if clinically indicated [see Warnings and Precautions (5.2)].

Contraception

Females

LUPRON DEPOT 3.75 mg may cause embryo-fetal harm when administered during pregnancy. LUPRON DEPOT 3.75 mg is not a contraceptive. If contraception is indicated, advise females of reproductive potential to use a non-hormonal method of contraception during treatment with LUPRON DEPOT 3.75 mg [see Warnings and Precautions (5.2)].

Infertility

Based on its pharmacodynamic effects of decreasing secretion of gonadal steroids, fertility is expected to be decreased while on treatment with LUPRON DEPOT 3.75 mg. Clinical and pharmacologic studies in adults (>18 years) with leuprolide acetate and similar analogs have shown reversibility of fertility suppression when the drug is discontinued after continuous administration for periods of up to 24 weeks [see Clinical Pharmacology (12.1)].

There is no evidence that pregnancy rates are affected following discontinuation of LUPRON DEPOT 3.75 mg.

Animal studies (prepubertal and adult rats and monkeys) with leuprolide acetate and other GnRH analogs have shown functional recovery of fertility suppression.

8.4 Pediatric Use

Safety and effectiveness of LUPRON DEPOT 3.75 mg for management of endometriosis and the preoperative hematologic improvement of women with anemia caused by fibroids have been established in females of reproductive age. Efficacy is expected to be the same for postpubertal adolescents under the age of 18 as for users 18 years and older. The safety and effectiveness of LUPRON DEPOT 3.75 mg for these indications have not been established in premenarcheal pediatric patients.

8.5 Geriatric Use

LUPRON DEPOT 3.75 mg is not indicated in postmenopausal women and has not been studied in this population.

11 DESCRIPTION

Leuprolide acetate is a synthetic nonapeptide analog of gonadotropin-releasing hormone [GnRH or luteinizing hormone releasing hormone (LH-RH)], a GnRH agonist. The chemical name is 5- oxo-L-prolyl-L-histidyl-L-tryptophyl-L-seryl-L-tyrosyl-D-leucyl-L-leucyl-L-arginyl-N-ethyl-L-prolinamide acetate (salt) with the following structural formula:

LUPRON DEPOT 3.75 mg (leuprolide acetate for depot suspension for injection) is available in a prefilled dual-chamber syringe containing sterile lyophilized microspheres powder which, when mixed with diluent, become a suspension intended as an IM injection.

The front chamber of LUPRON DEPOT 3.75 mg prefilled dual-chamber syringe contains leuprolide acetate for depot suspension (3.75 mg), purified gelatin (0.65 mg), DL-lactic and glycolic acids copolymer (33.1 mg) and D-mannitol (6.6 mg). The second chamber of diluent contains carboxymethylcellulose sodium (5 mg), D-mannitol (50 mg), polysorbate 80 (1 mg), water for injection, USP, and glacial acetic acid, USP to control pH.

During the manufacture of LUPRON DEPOT 3.75 mg, acetic acid is lost, leaving the peptide.

12 CLINICAL PHARMACOLOGY

12.1 Mechanism of Action

Leuprolide acetate is a long-acting GnRH analog. A single monthly injection of LUPRON DEPOT 3.75 mg results in an initial stimulation followed by a prolonged suppression of pituitary gonadotropins. Repeated dosing of LUPRON DEPOT 3.75 mg at monthly intervals results in decreased secretion of gonadal steroid. Consequently, tissues and functions that depend on gonadal steroids for their maintenance become quiescent. This effect is reversible on discontinuation of drug therapy.

Leuprolide acetate is not active when given orally.

12.2 Pharmacodynamics

Administration of LUPRON DEPOT 3.75 mg in therapeutic doses results in suppression of the pituitary-gonadal system. Normal function is usually restored within three months after treatment is discontinued. Therefore, diagnostic tests of pituitary gonadotropic and gonadal functions conducted during treatment and for up to three months after discontinuation of LUPRON DEPOT 3.75 mg may be affected.

12.3 Pharmacokinetics

Absorption

Following a single IM injection of LUPRON DEPOT 3.75 mg in healthy female volunteers, absorption of leuprolide was characterized by an initial increase in plasma concentration, with peak concentration ranging from 4.6 to 10.2 ng/mL at four hours postdosing. However, intact leuprolide and an inactive metabolite could not be distinguished by the assay used in the study. Following the initial rise, leuprolide concentrations started to plateau within two days after dosing and remained relatively stable for about four to five weeks with plasma concentrations of about 0.30 ng/mL.

Distribution

The mean steady-state volume of distribution of leuprolide following intravenous bolus administration to healthy male volunteers was 27 L. In vitro binding to human plasma proteins ranged from 43% to 49%.

Metabolism

Leuprolide acetate is a peptide that is primarily degraded by peptidase. In healthy male volunteers, a 1 mg bolus of leuprolide administered intravenously revealed that the mean systemic clearance was 7.6 L/h, with a terminal elimination half-life of approximately 3 hours based on a two-compartment model.

The major metabolite (M-I, a pentapeptide) plasma concentrations measured in 5 prostate cancer patients reached maximum concentration 2 to 6 hours after dosing and were approximately 6% of the peak parent drug concentration. One week after dosing, mean plasma M-I concentrations were approximately 20% of mean leuprolide concentrations.

Excretion

Following administration of LUPRON DEPOT 3.75 mg to 3 patients, less than 5% of the dose was recovered as parent and M-I metabolite in the urine.

Use in Specific Populations

The pharmacokinetics of LUPRON DEPOT have not been evaluated in patients with hepatic and renal impairment.

Drug Interactions

No pharmacokinetic drug-drug interaction studies have been conducted with LUPRON DEPOT 3.75 mg. However, leuprolide acetate is a peptide that is not degraded by cytochrome P-450 enzymes; hence, drug interactions associated with cytochrome P-450 enzymes would not be expected to occur.

13 NONCLINICAL TOXICOLOGY

13.1 Carcinogenesis, Mutagenesis, Impairment of Fertility

A two-year carcinogenicity study was conducted in rats and mice. In rats, a dose-related increase of benign pituitary hyperplasia and benign pituitary adenomas was noted at 24 months when the drug was administered subcutaneously at high daily doses (0.6 to 4 mg/kg). There was a significant but not dose-related increase of pancreatic islet-cell adenomas in females and of testicular interstitial cell adenomas in males (highest incidence in the low dose group). In mice, no leuprolide acetate-induced tumors or pituitary abnormalities were observed at a dose as high as 60 mg/kg for two years. Patients have been treated with leuprolide acetate for up to three years with doses as high as 10 mg/day and for two years with doses as high as 20 mg/day without demonstrable pituitary abnormalities.

Mutagenicity studies have been performed with leuprolide acetate using bacterial and mammalian systems. These studies provided no evidence of a mutagenic potential.

14 CLINICAL STUDIES

The safety and efficacy of LUPRON DEPOT 3.75 mg for the indicated populations has been established based on adequate and well-controlled studies in adults (See Table 8) of LUPRON DEPOT 3.75 mg [see Indications and Usage (1)].

14.1 Endometriosis

LUPRON DEPOT 3.75 mg Monotherapy

In controlled clinical studies, LUPRON DEPOT 3.75 mg monthly for six months was shown to be comparable to danazol 800 mg/day in relieving the clinical sign/symptoms of endometriosis (pelvic pain, dysmenorrhea, dyspareunia, pelvic tenderness, and induration) and in reducing the size of endometrial implants as evidenced by laparoscopy.

The clinical significance of a decrease in endometriotic lesions is not known, and laparoscopic staging of endometriosis does not necessarily correlate with the severity of symptoms.

LUPRON DEPOT 3.75 mg monthly induced amenorrhea in 74% and 98% of the women after the first and second month of treatment, respectively. Most of the remaining women reported episodes of only light bleeding or spotting. In the first, second and third post-treatment months, normal menstrual cycles resumed in 7%, 71% and 95% of women, respectively, excluding those who became pregnant.

Figure 1 illustrates the percent of women with symptoms at baseline, final treatment visit and sustained relief at 6 and 12 months following discontinuation of treatment for the various symptoms evaluated during the two controlled clinical studies. A total of 166 women received LUPRON DEPOT 3.75 mg. Seventy-five percent (N=125) of these elected to participate in the follow-up period. Of these women, 36% and 24% are included in the 6-month and 12-month follow-up analysis, respectively. All the women who had a pain evaluation at baseline and at least of one treatment visit are included in the Baseline (B) and final treatment visit (F) analysis.

Figure 1. Percent of Women with Signs/Symptoms of Endometriosis at Baseline, Final Treatment Visit, and After 6 and 12 Months of Follow-Up, LUPRON DEPOT 3.75 mg Monthly for Six Months

LUPRON DEPOT with Norethindrone Acetate Add-Back Therapy

Two clinical studies with treatment duration of 12 months were conducted to evaluate the effect of co-administration of LUPRON DEPOT 3.75 mg and norethindrone acetate on the loss of bone mineral density (BMD) associated with LUPRON DEPOT 3.75 mg and on the efficacy of LUPRON DEPOT in relieving symptoms of endometriosis. All women in these studies received calcium supplementation with 1000 mg elemental calcium. A total of 242 women were treated with monthly administration of LUPRON DEPOT 3.75 mg (13 injections) and 191 of them were co-administered 5 mg norethindrone acetate taken daily. The population age range was 17-43 years old. The majority of women were Caucasian (87%).

One co-administration study was a controlled, randomized and double-blind study included 51 women treated monthly with LUPRON DEPOT 3.75 mg alone and 55 women treated monthly with LUPRON DEPOT 3.75 mg plus norethindrone acetate daily. Women in this trial were followed for up to 24 months after completing one year of treatment. The other study was an open-label single arm clinical study in 136 women of one year of treatment with LUPRON DEPOT 3.75 mg monthly and daily norethindrone acetate 5 mg, with follow-up for up to 12 months after completing treatment. See Table 8.

The assessment of efficacy was based on the investigator’s or the woman’s monthly assessment of five signs or symptoms of endometriosis (dysmenorrhea, pelvic pain, deep dyspareunia, pelvic tenderness and pelvic induration).

Table 8 below provides detailed efficacy data regarding relief of symptoms of endometriosis based on the two studies of co-administration of LUPRON DEPOT 3.75 mg monthly and norethindrone acetate 5 mg daily.

Table 8. Effect of LUPRON DEPOT and Norethindrone Acetate on the Symptoms of Endometriosis and Mean Clinical Severity Scores
 |  |  | Percent of Women with Symptoms |  |  | Clinical Pain Severity Score
 |  |  | Baseline |  | Final | Baseline |  | Final
Variable | Study | Group | N^1 | (%)^2 | (%) | N^1 | Value^3 | Change
Dysmenorrhea | Controlled Study | LD*^4 | 51 | (100) | (4) | 50 | 3.2 | -2.0
 |  | LD/N† | 55 | (100) | (4) | 54 | 3.1 | -2.0
 | Open Label Study | LD/N^5 | 136 | (99) | (9) | 134 | 3.3 | -2.1
Pelvic Pain | Controlled Study | LD^4 | 51 | (100) | (66) | 50 | 2.9 | -1.1
 |  | LD/N | 55 | (96) | (56) | 54 | 3.1 | -1.1
 | Open Label Study | LD/N^5 | 136 | (99) | (63) | 134 | 3.2 | -1.2
Deep Dyspareunia | Controlled Study | LD^4 | 42 | (83) | (37) | 25 | 2.4 | -1.0
 |  | LD/N | 43 | (84) | (45) | 30 | 2.7 | -0.8
 | Open Label Study | LD/N^5 | 102 | (91) | (53) | 94 | 2.7 | -1.0
Pelvic Tenderness | Controlled Study | LD^4 | 51 | (94) | (34) | 50 | 2.5 | -1.0
 |  | LD/N | 54 | (91) | (34) | 52 | 2.6 | -0.9
 | Open Label Study | LD/N^5 | 136 | (99) | (39) | 134 | 2.9 | -1.4
Pelvic Induration | Controlled Study | LD^4 | 51 | (51) | (12) | 50 | 1.9 | -0.4
 |  | LD/N | 54 | (46) | (17) | 52 | 1.6 | -0.4
 | Open Label Study | LD/N^5 | 136 | (75) | (21) | 134 | 2.2 | -0.9
* LD = LUPRON DEPOT 3.75 mg assessment
† LD/N = LUPRON DEPOT 3.75 mg plus norethindrone acetate 5 mg
^1 Number of women that were included in the assessment
^2 Percentage of women with the symptom/sign
^3 Value description: 1=none; 2= mild; 3= moderate; 4= severe
^4 12-month treatment followed by up to 24 months of follow up
^5 12-month treatment followed by up to 12 months of follow up

Suppression of menses (menses was defined as three or more consecutive days of menstrual bleeding) was maintained throughout treatment in 84% and 73% of women receiving leuprolide acetate and norethindrone acetate, in the controlled study and open label study, respectively. The median time for menses resumption after treatment with leuprolide acetate and norethindrone acetate was 8 weeks.

Changes in Bone Density

The effect of LUPRON DEPOT 3.75 mg and norethindrone acetate on bone mineral density was evaluated by dual energy x-ray absorptiometry (DEXA) scan in the two clinical trials. For the open-label study, success in mitigating BMD loss was defined as the lower bound of the 95% confidence interval around the change from baseline at one year of treatment not to exceed -2.2%. The bone mineral density data of the lumbar spine from these two studies are presented in Table 9.

Table 9. Mean Percent Change from Baseline in Bone Mineral Density of Lumbar Spine
 | LUPRON DEPOT 3.75 mg (LD only) |  | LUPRON DEPOT 3.75 mg plus norethindrone acetate 5 mg daily (LD/N)
 | Controlled Study |  | Controlled Study |  | Open Label Study
 | N | Change Mean (95% CI)# | N | Change Mean (95% CI)# | N | Change Mean (95% CI)#
Week 24* | 41 | -3.2% (-3.8, -2.6) | 42 | -0.3% (-0.8, 0.3) | 115 | -0.2% (-0.6, 0.2)
Week 52† | 29 | -6.3% (-7.1, -5.4) | 32 | -1.0% (-1.9, -0.1) | 84 | -1.1% (-1.6, -0.5)
* Includes on-treatment measurements that fell within 2 to 252 days after the first day of treatment.
† Includes on-treatment measurements >252 days after the first day of treatment.
# 95% CI: 95% Confidence Interval

The change in BMD following discontinuation of treatment is shown in Table 10.

Table 10. Mean Percent Change from Baseline in BMD of Lumbar Spine in Post-Treatment Follow-up Period^1
Post Treatment Measurement | Controlled Study |  |  |  |  |  | Open Label Study
 | LD-Only |  |  | LD/N |  |  | LD/N
 | N | Mean % Change | 95% CI (%)^2 | N | Mean % Change | 95% CI (%) | N | Mean % Change | 95% CI (%)^2
Month 8 | 19 | -3.3 | (-4.9, -1.8) | 23 | -0.9 | (-2.1, 0.4) | 89 | -0.6 | (-1.2, 0.0)
Month 12 | 16 | -2.2 | (-3.3, -1.1) | 12 | -0.7 | (-2.1, 0.6) | 65 | 0.1 | (-0.6, 0.7)
^1 Patients with post treatment measurements
^2 95% CI (2-sided) of percent change in BMD values from baseline

These clinical studies demonstrated that co-administration of leuprolide acetate and norethindrone acetate 5 mg daily is effective in significantly reducing the loss of bone mineral density that occurs with LUPRON DEPOT 3.75 mg and in relieving symptoms of endometriosis.

14.2 Fibroids

LUPRON DEPOT 3.75 mg monthly for a period of three to six months was studied in four controlled clinical trials.

In one of these clinical studies, enrollment was based on hematocrit ≤ 30% and/or hemoglobin ≤ 10.2 g/dL. Administration of LUPRON DEPOT 3.75 mg monthly, concomitantly with iron, produced an increase of ≥ 6% hematocrit and ≥ 2 g/dL hemoglobin in 77% of women at three months of therapy. The mean change in hematocrit was 10.1% and the mean change in hemoglobin was 4.2 g/dL. Clinical response was judged to be a hematocrit of ≥ 36% and hemoglobin of ≥ 12 g/dL, thus allowing for autologous blood donation prior to surgery. At two and three months, respectively, 71% and 75% of women met this criterion (Table 11). These data suggest however, that some women may benefit from iron alone or 1 to 2 months of LUPRON DEPOT 3.75 mg.

Table 11. Percent of Women Achieving Hematocrit ≥ 36% and Hemoglobin ≥ 12 g/dL
Treatment Group | Week 4 | Week 8 | Week 12
LUPRON DEPOT 3.75 mg with Iron (N=104) | 40* | 71† | 75*
Iron Alone (N=98) | 17 | 39 | 49
* P-Value < 0.01
† P-Value < 0.001

Excessive vaginal bleeding (menorrhagia or menometrorrhagia) decreased in 80% of women at three months. Episodes of spotting and menstrual-like bleeding were noted in 16% of women at final visit.

In this same study, a decrease in uterine volume and myoma volume of ≥25% was seen in 60% and 54% of women, respectively. The mean fibroid diameter was 6.3 cm at pretreatment and decreased to 5.6 cm at the end of treatment. LUPRON DEPOT 3.75 mg was found to relieve symptoms of bloating, pelvic pain, and pressure.

In three other controlled clinical trials, enrollment was not based on hematologic status. Mean uterine volume decreased by 41% and myoma volume decreased by 37% at final visit as evidenced by ultrasound or MRI. The mean fibroid diameter was 5.6 cm at pretreatment and decreased to 4.7 cm at the end of treatment. These women also experienced a decrease in symptoms including excessive vaginal bleeding and pelvic discomfort. Ninety-five percent of these women became amenorrheic with 61%, 25%, and 4% experiencing amenorrhea during the first, second, and third treatment months respectively.

In addition, post-treatment follow-up was carried out in one clinical trial for a small percentage of women on LUPRON DEPOT 3.75 mg (N=46) among the 77% who demonstrated a ≥ 25% decrease in uterine volume while on therapy. Menses usually returned within two months of cessation of therapy. Mean time to return to pretreatment uterine size was 8.3 months. Regrowth did not appear to be related to pretreatment uterine volume.

Changes in Bone Density

In one of the studies for fibroids described above, when LUPRON DEPOT 3.75 mg was administered for three months in women with uterine fibroids, vertebral trabecular bone mineral density, as assessed by quantitative digital radiography (QDR), revealed a mean decrease of 2.7% compared with baseline. Six months after discontinuation of therapy, a trend toward recovery was observed.

16 HOW SUPPLIED/STORAGE AND HANDLING

Each LUPRON DEPOT 3.75 mg kit (NDC 0074-3641-03) contains:

- one prefilled dual-chamber syringe
- one plunger
- two alcohol swabs

Each single-dose dual chamber syringe contains sterile white lyophilized microsphere powder of 3.75 mg of leuprolide acetate incorporated in a biodegradable polymer in one chamber and a colorless diluent (1 mL) in the other chamber. When mixed with the diluent, LUPRON DEPOT 3.75 mg for injection, is administered as a single IM injection.

Store between 20° to 25°C (68° to 77°F). Excursions permitted to 15° to 30°C (59° to 86°F) [see USP Controlled Room Temperature].

17 PATIENT COUNSELING INFORMATION

Loss of Bone Density

Advise patients about the risk of loss of bone mineral density and that treatment is limited [see Dosage and Administration (2.1)]. Advise patients about other factors that can increase and decrease their risk of bone mineral density loss [see Warnings and Precautions (5.1)].

Embryo-Fetal Toxicity

- Advise females of reproductive potential of the possible risk to a fetus. Advise patients to inform healthcare provider of a known or suspected pregnancy [see Warnings and Precautions (5.2) and Use in Special Populations (8.1)].
- If contraception is indicated, advise females of reproductive potential to use non-hormonal contraception during treatment with LUPRON DEPOT 3.75 mg [see Use in Special Populations (8.3)].

Severe Cutaneous Adverse Reactions

Inform patients that severe cutaneous adverse reactions (SCARs) may occur during treatment with LUPRON DEPOT 3.75 mg. Advise patients to discontinue LUPRON DEPOT 3.75 mg and immediately contact their healthcare provider if they experience signs or symptoms of SCARs [see Warnings and Precautions (5.3)].

Hypersensitivity Reactions

Inform patients that hypersensitivity reactions, including anaphylaxis, have been reported with LUPRON DEPOT. Advise patients to seek appropriate medical care if symptoms of hypersensitivity reactions occur [see Warnings and Precautions (5.4) and Adverse Reactions (6.2)].

Initial Flare of Symptoms

Advise patients that they may experience an increase in symptoms during the initial days of therapy. Advise patients that these symptoms should dissipate with continued therapy [see Warnings and Precautions (5.5)].

Convulsions

Inform patients that convulsions have been reported in patients who have received LUPRON DEPOT. Advise patients to seek medical attention in the event of a convulsion [see Warnings and Precautions (5.6)].

Clinical Depression

Inform patients that depression may occur or worsen during treatment with GnRH agonists, including LUPRON DEPOT 3.75 mg, especially in patients with a history of depression. Advise patients to immediately report thoughts and behaviors of concern to healthcare providers [see Warnings and Precautions (5.7)].

Manufactured for
AbbVie Inc.
North Chicago, IL 60064
by Takeda Pharmaceutical Company Limited
Osaka, Japan 540-8645

Revised 09/2025

20085416

PRINCIPAL DISPLAY PANEL

NDC 0074-3641-03

FOR ADULT USE 3.75 mg for 1 - Month administration

Single Dose Administration Kit with prefilled dual-chamber syringe.

LupronDepot®

(leuprolide acetate for depot suspension)

3.75 mg for 1 - Month administration

FOR INTRAMUSCULAR INJECTION

The front chamber contains: leuprolide acetate 3.75 mg, purified gelatin 0.65 mg, DL-lactic & glycolic acids copolymer 33.1 mg, D-mannitol 6.6 mg

The second chamber contains: D-mannitol 50 mg, carboxymethylcellulose sodium 5 mg, polysorbate 80 1 mg, water for injection, USP, and glacial acetic acid, USP to control pH

Rx only